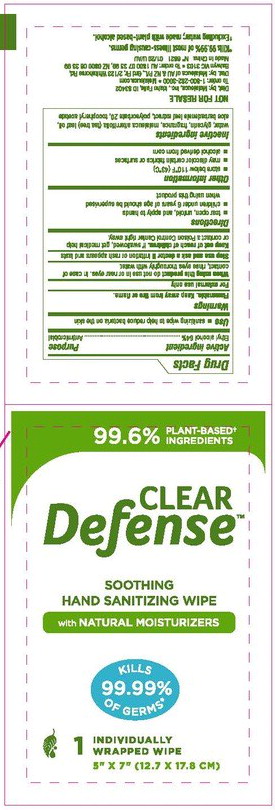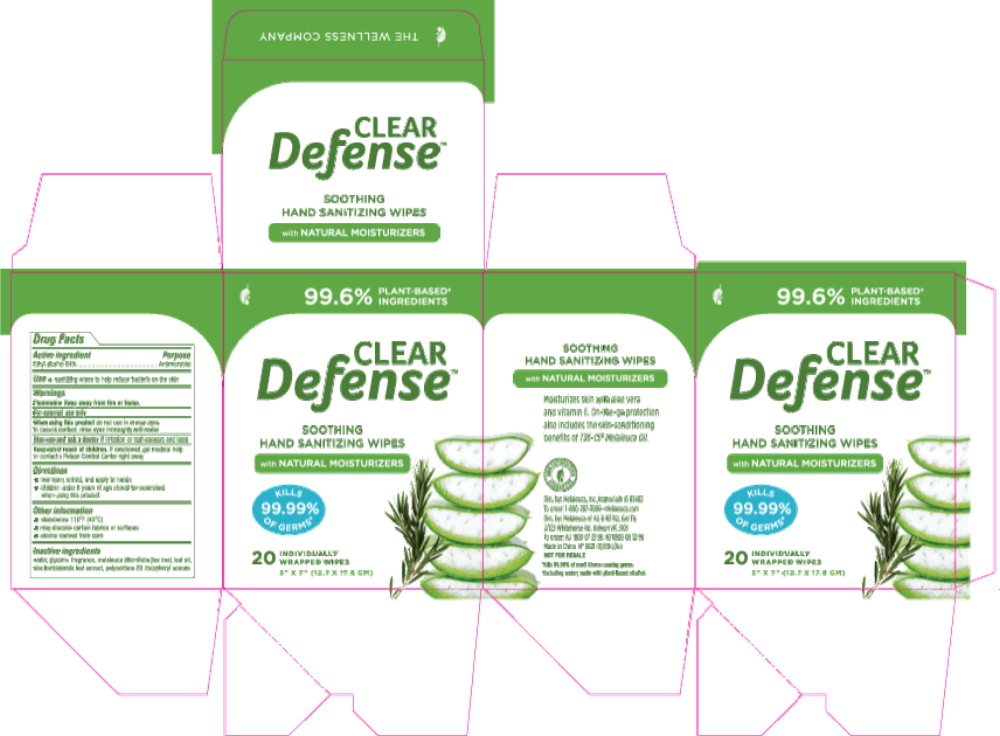 DRUG LABEL: Clear Defense
NDC: 54473-142 | Form: CLOTH
Manufacturer: Melaleuca, Inc.
Category: otc | Type: HUMAN OTC DRUG LABEL
Date: 20180223

ACTIVE INGREDIENTS: ALCOHOL 3.32 g/1 1
INACTIVE INGREDIENTS: WATER; GLYCERIN; TEA TREE OIL; ALOE VERA LEAF; POLYSORBATE 20; .ALPHA.-TOCOPHEROL ACETATE

Clear Defense Wipes Content of Label

Active ingredient
Ethyl alcohol 64%

Purpose
Antimicrobial

Warnings
Flammable. Keep away from fire or flame.
Foe external use only

When using this product do not use in or near eyes. In case of contact, rinse eyes thoroughly with water.

Stop use and ask a doctor if irritation or rash appears and lasts

Keep out of reach of children. If swallowed, get medical help or contact a Poison Control Center right away.

Directions

- Tear open, unfold, and apply to hands
- children under 6 years of age should be supervised when using this product

Other information

- store below 110°F (43°C)

Other information

- may discolor certain fabrics or surfaces

Inactive ingredients
water, glycerin, fragrance, melaleuca alternifolia (tea tree) oil (T36-C5® brand), aloe barbadensis leaf extract, polysorbate 20, tocopheryl acetate

Use

- sanitizing wipes to help reduce bacterial on the skin

Principal Display Panel – Packet Label

99.6% PLANT-BASED
INGREDIENTS

CLEAR
Defense™

SOOTHING

HAND SANITIZING WIPE

with NATURAL MOISTURIZERS

KILLS
99.99%
OF GERMS

1 INDIVIDUALLY
WRAPPED WIPE

5” x 7” (12.7 x 17.8 CM)

Principal Display Panel – Carton Label

99.6% PLANT-BASED
INGREDIENTS

CLEAR
Defense™

SOOTHING

HAND SANITIZING WIPE

with NATURAL MOISTURIZERS

KILLS
99.99%
OF GERMS

20 INDIVIDUALLY
WRAPPED WIPES

5” x 7” (12.7 x 17.8 CM)